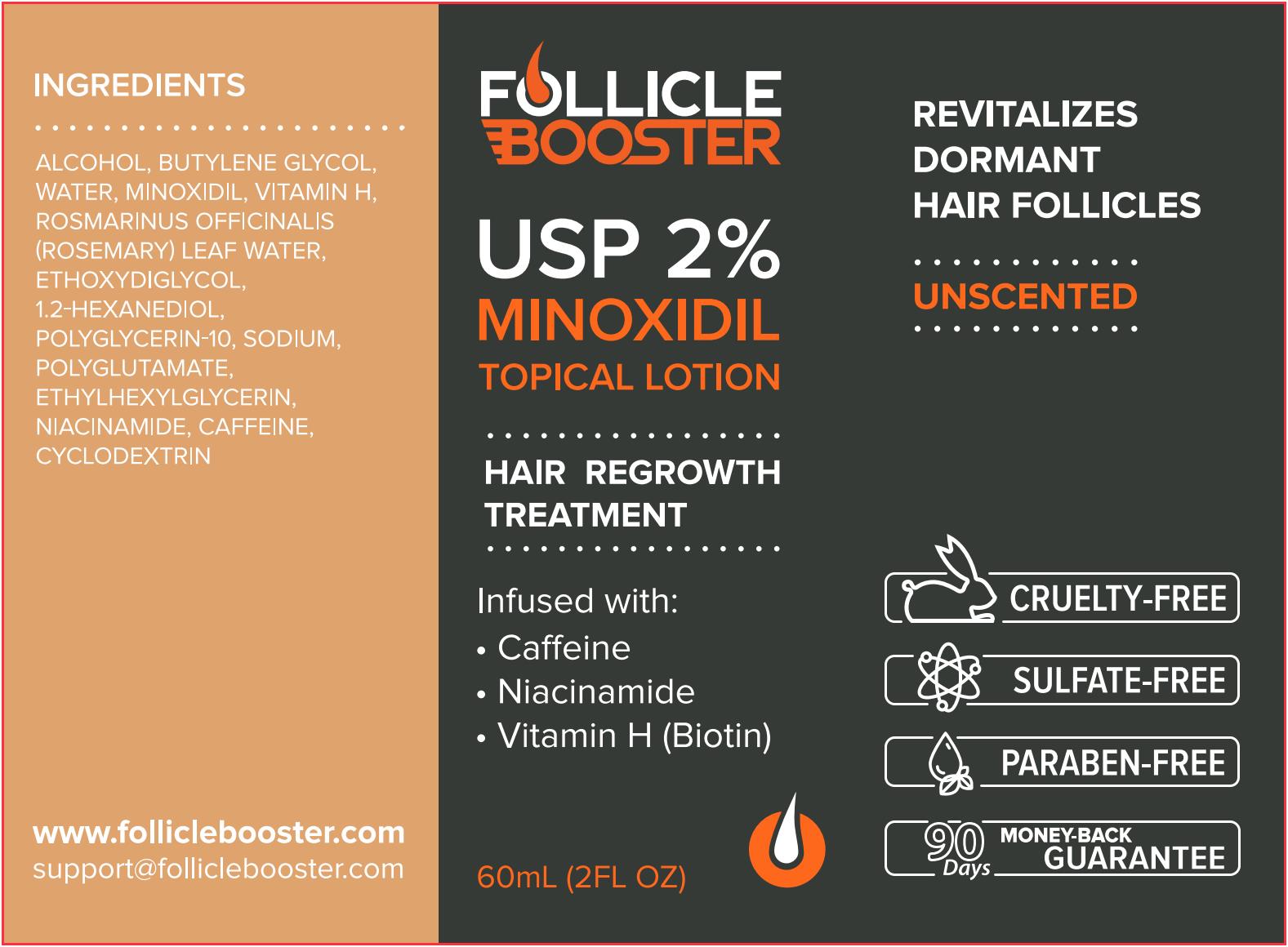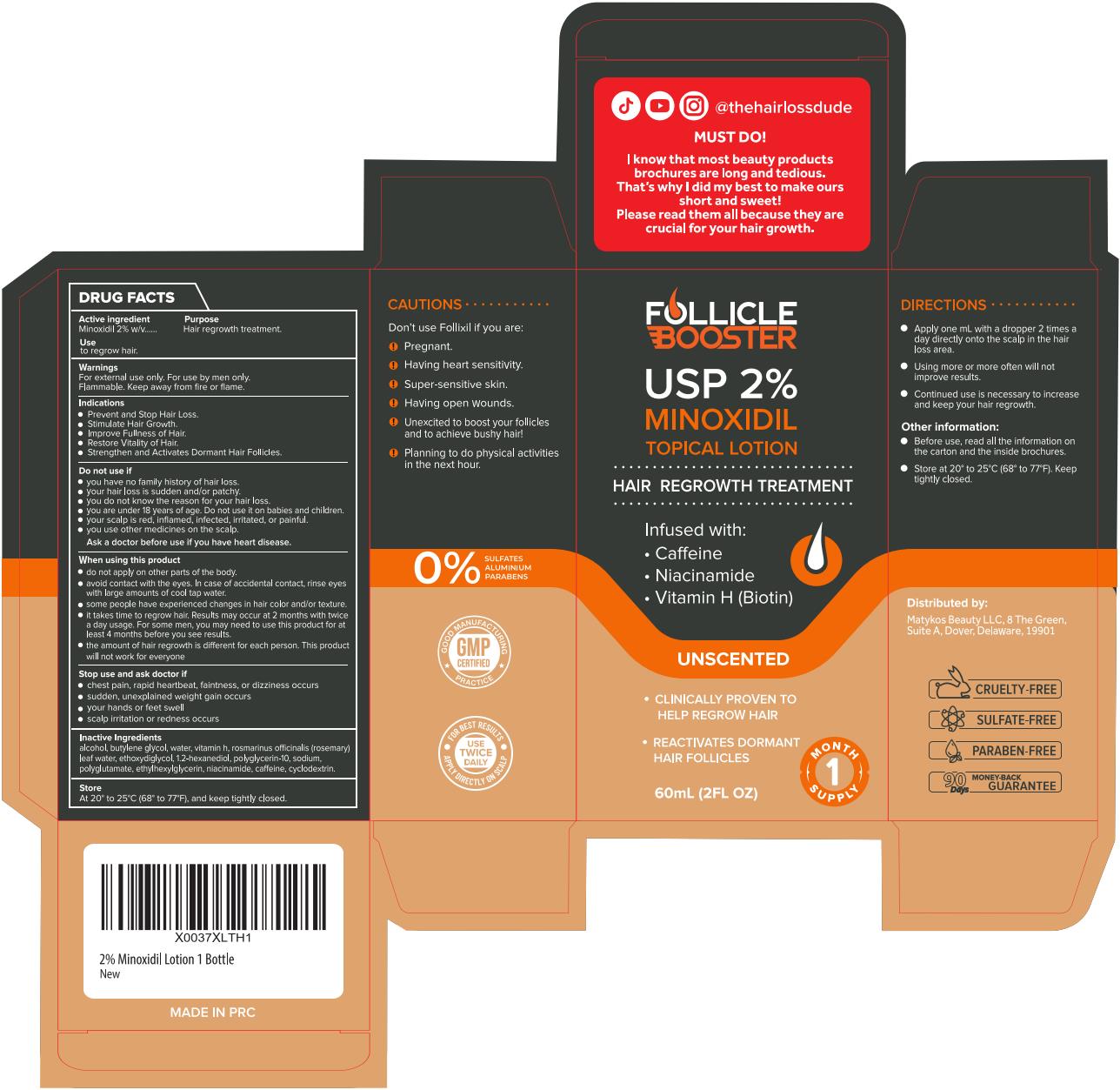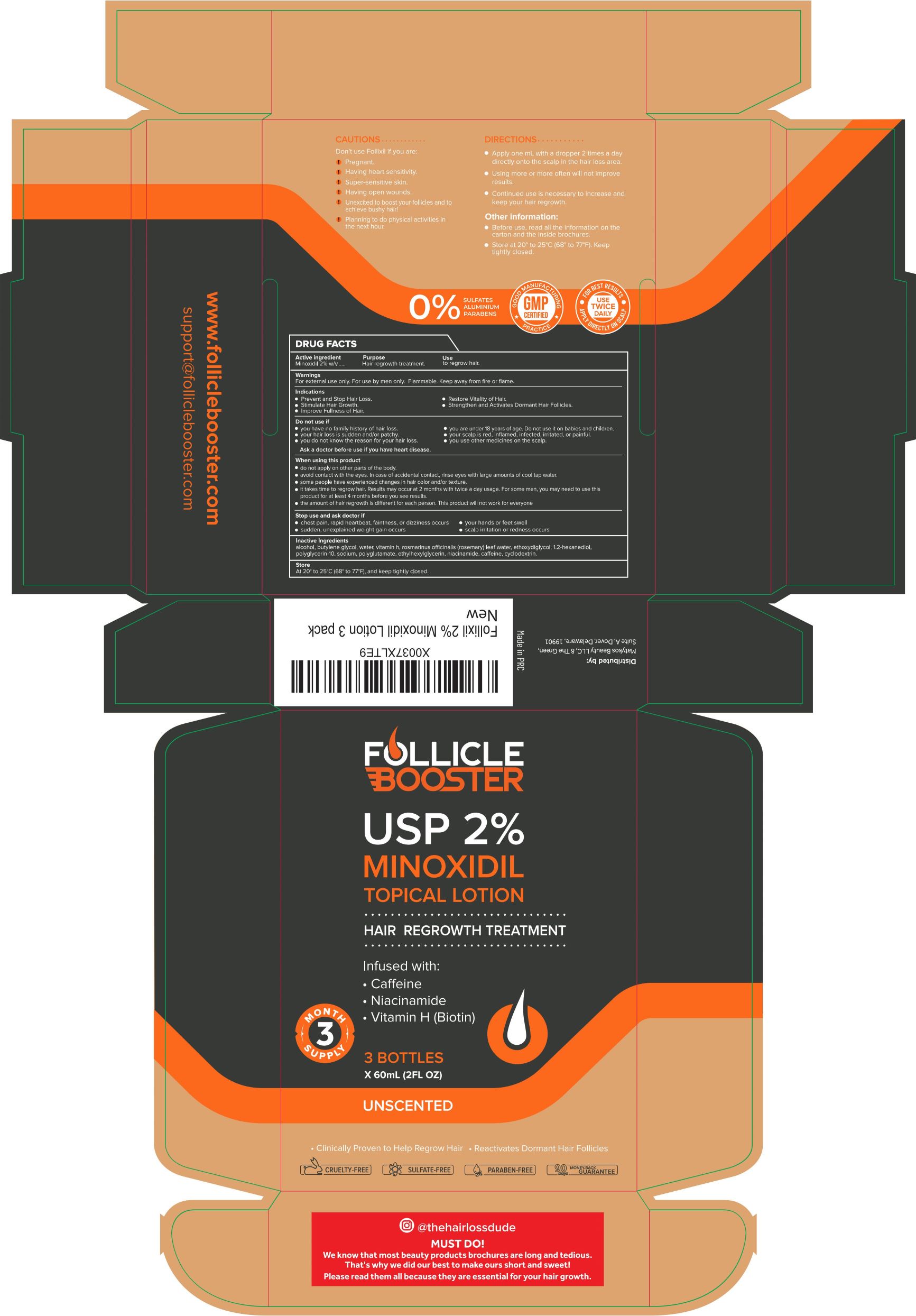 DRUG LABEL: FOLLIXIL Hair Regrowth Treatment
NDC: 83835-231 | Form: LIQUID
Manufacturer: Matykos Beauty LLC
Category: otc | Type: HUMAN OTC DRUG LABEL
Date: 20240227

ACTIVE INGREDIENTS: MINOXIDIL 2 g/100 mL
INACTIVE INGREDIENTS: ALCOHOL; BUTYLENE GLYCOL; CAFFEINE; CYCLODEXTRINS; BIOTIN; ROSMARINUS OFFICINALIS FLOWERING TOP OIL; NIACINAMIDE; WATER; 1,2-HEXANEDIOL; DIETHYLENE GLYCOL MONOETHYL ETHER; ETHYLHEXYLGLYCERIN; POLYGLYCERIN-10; SODIUM; POLYGLYCOLIC ACID

FoB 2% Lotion

Active ingredient

Minoxidil 2% w/v

Purpose

Hair regrowth treatment

Use

to regrowth hair.

Warnings

For external use only. For use by men only.

Flammable. Keep away from fire or flame.

Indications

- Prevent and Stop Hair Loss.
- Stimulate Hair Growth.
- Improve Fullness of Hair.
- Restore Vitality of Hair.
- Strengthen and Activates Dormant Hair Follicles.

Do not use if

- you have no family histoy of hair loss.
- your hair loss is sudden and/or patchy.
- you do not know the reason for your hair loss.
- you are under 18 years of age. Do not use if on babies and children.
- your scalp is red, inflamed, infected, irritated, or painful.
- you use other medicines on the scalp.

Ask a doctor before use if you have heart disease.

When using this product

- do not apply on other parts of the body.
- avoid contact with the eyes. In case of accidental contact, rinse eyes with large amounts of cool tap water.
- some people have experienced changes in hair color and/or texture.
- it takes time to regrow hair. Results may occur at 2 months with twice a day usage. For some men, you may need to use this product for at least 4 months before you see results.
- the amount of hair regrowth is different for each person. This product will not work for everyone.

Stop use and ask doctor if

- chest pain, rapid heartbeat, faintness, or dizziness occurs
- sudden, unexplained weight gain occurs
- your hands or feet swell
- scalp irritation or redness occurs

Do not use it on babies and children.

Inactive Ingredients

alcohol, butylene glycol, water, vitamin h, rosmarinus officinalis (rosemary) leaf water, ethoxydiglycol, 1.2-hexanediol, polyglycerin-10, sodium, polyglutamate, ethylhexylglycerin, niacinamide, caffeine, cyclodextrin.

Store

at 20 to 25℃ (68 to 77℉), and keep tightly closed.

CAUTIONS

Don't use Follixil if you are:

- Pregnant.
- Having heart sensitivity.
- Super-sensitive skin.
- Having open wounds.
- Unexcited to boost your follicles and to achieve bushy hair!
- Planning to do physical activities in the next hour.

DIRECTIONS

- Apply one mL with a dropper 2 times a day directly onto the scalp in the hair loss area.
- Using more or more often will not improve results.
- Continued use is necessary to increase and keep your hair regrowth.

Other information:

- Before use, read all the information on the carton and the inside brochures.
- Store at 20 to 25℃ (68 to 77℉). Keep tightly closed.